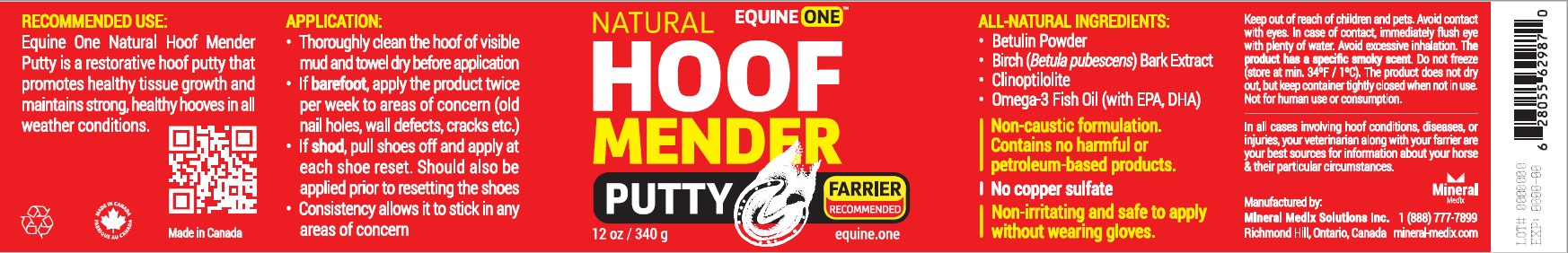 DRUG LABEL: Equine One Hoof Mender Putty
NDC: 86142-002 | Form: OINTMENT
Manufacturer: Mineral Medix Solutions Inc
Category: animal | Type: OTC ANIMAL DRUG LABEL
Date: 20221221

ACTIVE INGREDIENTS: BETULA PUBESCENS BARK 5.00 g/100 g; BETULIN 0.25 g/100 g; OMEGA-3 FATTY ACIDS 19.75 g/100 g; CLINOPTILOLITE 75.00 g/100 g

ACTIVE INGREDIENT

Omega-3 Fatty Acid, Betula Pubescens Bark, Betulin, Clinoptilolite

PURPOSE

Topical hoof putty to help with most common hoof related issues

USE

Equine One Hoof Mender Putty is a unique restorative hoof putty based on Birch Bark Extract, Betulin, Clinoptilolite, Omega 3 with Vitamins A & D for professional care of horses' hooves. It is a non-caustic product easily applied to the white line, hoof wall separations, and the hoof frog.

- Restores strong and healthy hooves in all weather conditions
- Maintains a germ-free hoof environment-helps avoid crumbling horn, white line disease, and thrush
- Non-irritating and safe to apply without wearing gloves
- The product does not dry out, but keep container tightly closed when not in use
- Can be used under pads to keep soles and frogs in healthy condition
- Can be used for horses, ponies, donkeys and other hooved animals
- Made with a non-caustic formulation—contains no copper sulfate, no harmful or petroleum-based products
- Please note the equine care product is for hoof use only.
- The product has a distinctive smoky smell

WARNINGS

FOR HOOF USE ONLY

Keep out of reach of children and pets.

Avoid contact with eyes.

In case of contact, immediately flush eye with plenty of water.

Avoid excessive inhalation.

Do not freeze (store at min. 34ºF / 1ºC).

Not for human use or consumption.

In all cases involving hoof conditions, diseases, or injuries, your veterinarian along with your farrier are your best sources for information about your horse & their particular circumstances.

Application

Thoroughly clean the hoof of visible mud, and a towel dry before application

If barefoot, apply the product twice per week to areas of concern (old nail holes, wall defects, cracks etc.)

If shod, pull shoes off and apply during each shoe reset. Should also be applied prior to resetting the shoes

Use regularly as a preventative.